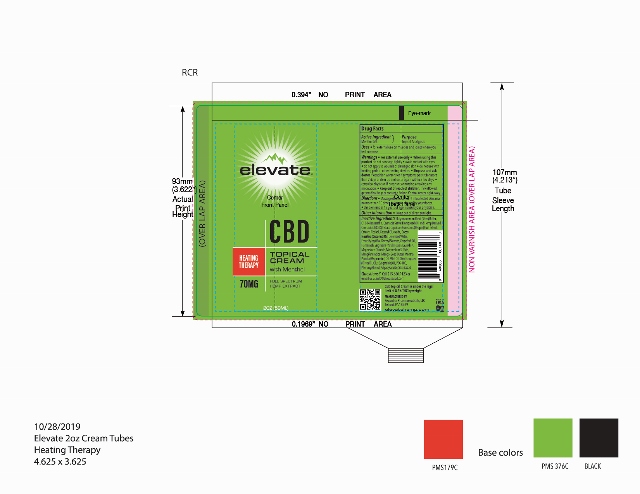 DRUG LABEL: elevate HEATING THERAPY
NDC: 76348-458 | Form: CREAM
Manufacturer: Renu Laboratories, Inc.
Category: otc | Type: HUMAN OTC DRUG LABEL
Date: 20220113

ACTIVE INGREDIENTS: MENTHOL 2.8 g/56 g
INACTIVE INGREDIENTS: CAPSICUM; GLYCERYL MONOSTEARATE; CETEARYL GLUCOSIDE; COCONUT OIL; WHITE WAX; SHEA BUTTER; C13-14 ISOPARAFFIN; CANNABIS SATIVA SEED OIL; CETOSTEARYL ALCOHOL; OLIVE OIL; STEARIC ACID; GRAPEFRUIT OIL; MAGNESIUM CHLORIDE; MAGNESIUM SULFATE, UNSPECIFIED; LAURETH-7; WITCH HAZEL; CANNABIDIOL; WATER; POLYETHYLENE GLYCOL 4500; CORN OIL; MANGIFERA INDICA SEED BUTTER; PEPPERMINT OIL; PHENOXYETHANOL; POLYACRYLAMIDE (10000 MW)

elevate HEATING THERAPY TOPICAL CREAM

ACTIVE INGREDIENT

Menthol 5 percent

Warnings

For external use only

When using this product do not bandage tightly

avoid contact with eye

do not apply to wounds or damaged skin

Stop use and ask doctor

if condition worsens or if symptoms persist for more than 7 days or clear up and occur again within a few days

Keep out of reach of children

If swallowed get medical help or contact Poison Control Center right away

Keep out of reach of children. If swallowed get medical help or contact a Poison Control center right away.

PURPOSE

Topical Analgesic

QUESTIONS

Call 215.660.9123 or email us at info@elevatecbd.com

DOSAGE AND ADMINISTRATION

Massage desired amount into affected skin area no more than 10 times daily or ask directed by your doctor.

Children under 12 years of age

consult your physician

OTHER SAFETY INFORMATION

Keep out of direct sunlight

INACTIVE INGREDIENT

Butyrospermum Parkii (Shea) Butter, C13-14 Isoparaffin, Cannabis Sativa (Hempseed) Oil and Hemp Derived Cannabidiol (CBD) Extract, Cetearyl Alcohol, Cetearyl Glucoside, Cocos Nucifera (Coconut) Oil, Deionized Water, Emulsifying Wax, Glyceryl Stearate, Grapefruit Oil, Hamamelis Virginiana (Witch Hazel), Laureth-7, Magnesium Chloride, Magnesium Sulfate, Mangifera Indica (Mango) Seed Butter, Mentha Piperita (Peppermint) Oil, Mint Oil, Olea Europaea (Olive) Oil, Olus (Vegetable) Oil, PEG-100, Phenoxyethanol, Polyacrylamide, Stearic Acid

STATEMENT OF IDENTITY

elevate

CBD

COOLING

THERAPY TOPICAL CREAM

Uses

for external use on muscles and joints where you feel stiffness

Keep out of reach of children

If swallowed get medical help or contact a Poison Control center right away

PACKAGE LABEL

2 oz. cream Heating Therapy tube